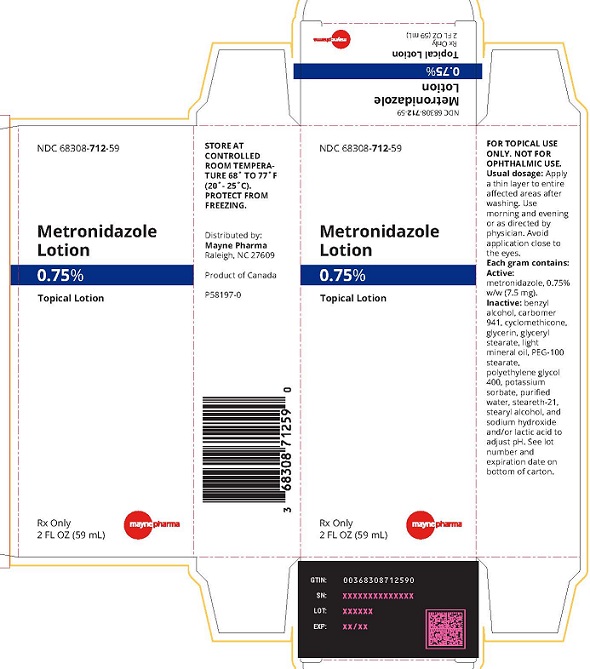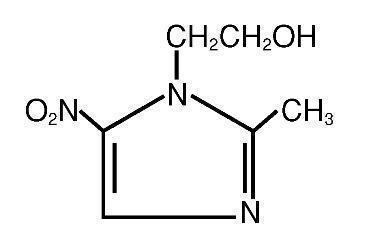 DRUG LABEL: metronidazole
NDC: 68308-712 | Form: LOTION
Manufacturer: Mayne Pharma Inc.
Category: prescription | Type: HUMAN PRESCRIPTION DRUG LABEL
Date: 20240930

ACTIVE INGREDIENTS: METRONIDAZOLE 7.5 mg/1 g
INACTIVE INGREDIENTS: BENZYL ALCOHOL; CARBOMER HOMOPOLYMER TYPE A; CYCLOMETHICONE; GLYCERIN; GLYCERYL MONOSTEARATE; LIGHT MINERAL OIL; PEG-100 STEARATE; POLYETHYLENE GLYCOL 400; POTASSIUM SORBATE; WATER; STEARETH-21; STEARYL ALCOHOL; SODIUM HYDROXIDE; LACTIC ACID

Metronidazole Topical Lotion, 0.75%
Rx only
FOR TOPICAL USE ONLY
(NOT FOR OPHTHALMIC USE)

DESCRIPTION

Metronidazole Topical Lotion contains metronidazole, USP, at a concentration of 7.5 mg per gram (0.75% w/w) in a lotion consisting of benzyl alcohol, carbomer 941, cyclomethicone, glycerin, glyceryl stearate, light mineral oil, PEG-100 stearate, polyethylene glycol 400, potassium sorbate, purified water, steareth-21, stearyl alcohol, and sodium hydroxide and/or lactic acid to adjust pH.

Metronidazole is an imidazole and is classified therapeutically as an antiprotozoal and antibacterial agent. Chemically, metronidazole is 2-methyl-5-nitro-1H-imidazole-1-ethanol. The molecular formula is C6H9N3O3 and molecular weight is 171.16. Metronidazole is represented by the following structural formula:

CLINICAL PHARMACOLOGY

The mechanisms by which metronidazole acts in the treatment of rosacea are unknown, but appear to include an anti-inflammatory effect.

Pharmacokinetics:

Absorption of metronidazole after topical application of Metronidazole Topical Lotion is less complete and more prolonged than after oral administration. Detectable plasma levels were found in all subjects following the administration of a 1 gram dose of Metronidazole Topical Lotion (containing 7.5 mg of metronidazole) applied every morning and evening for 4 days to the faces of 8 patients. The highest concentration (96 ng/mL) seen following the morning dose on Day 5 was approximately 80 times lower than the peak concentrations produced by a single 250 mg tablet of metronidazole. The mean (± SD) AUC0-24 after twice daily administration was 962 ± 373 ng.hr/mL.

INDICATIONS AND USAGE

Metronidazole Topical Lotion is indicated for topical application in the treatment of inflammatory papules and pustules of rosacea.

CLINICAL STUDIES

A controlled clinical study was conducted in 144 patients with moderate to severe rosacea, in which Metronidazole Topical Lotion was compared with its vehicle. Applications were made twice daily for 12 weeks during which patients were instructed to avoid spicy foods, thermally hot foods and drinks, alcoholic beverages, and caffeine. Patients were also provided samples of a soapless cleansing lotion and, if requested, a moisturizer. Metronidazole Topical Lotion was significantly more effective than its vehicle in mean percent reduction of inflammatory lesions associated with rosacea and in the investigators' global assessment of improvement. The results of the mean percent reduction in inflammatory lesion counts from baseline after 12 weeks of treatment and the investigators' global assessment of improvement at week 12 are presented in the following table:

Efficacy Outcomes at Week 12
Mean Percent reduction in Inflammatory Lesion Counts from Baseline
Metronidazole Topical Lotion N=65 |  |  |  | Vehicle Lotion N=60
55% |  |  |  | 20%
Investigators' Global Assessment of Improvement
(percent change from baseline)
 | Worse | No Change | Minimal Improvement | Definite Improvement | Marked Improvement | Clear
Metronidazole Topical Lotion N=65 | 5% | 12% | 11% | 32% | 32% | 8%
Vehicle Lotion N=60 | 15% | 27% | 23% | 15% | 20% | 0%

The scale is based on the following definitions:

Worse: Exacerbation of either erythema or quantitative assessment of papules and/or pustules.

No Change: Condition remains the same.

Minimal Improvement: Slight improvement in the quantitative assessment of papules and/or pustules, and/or slight improvement in erythema.

Definite Improvement: More pronounced improvement in the quantitative assessment of papules and/or pustules, and/or more pronounced improvement in erythema.

Marked Improvement: Obvious improvement in the quantitative assessment of papules and/or pustules, and/or obvious improvement in erythema.

Clear: No papules or pustules and minimal residual or no erythema.

CONTRAINDICATIONS

Metronidazole Topical Lotion is contraindicated in individuals with a history of hypersensitivity to metronidazole or to other ingredients of the formulation.

PRECAUTIONS

General:

Topical metronidazole formulations have been reported to cause tearing of the eyes. Therefore, contact with the eyes should be avoided. If a reaction suggesting local irritation occurs, patients should be directed to use the medication less frequently or discontinue use. Metronidazole is a nitroimidazole and should be used with care in patients with evidence or history of blood dyscrasia.

Information for Patients:

Patients using Metronidazole Topical Lotion should receive the following information and instructions:

1. This medication is to be used only as directed by the physician.
2. It is for external use only.
3. Avoid contact with the eyes.
4. Cleanse affected area(s) before applying this medication.
5. Patients should report any adverse reaction to their physician.

Drug Interactions:

Oral metronidazole has been reported to potentiate the anticoagulant effect of warfarin and coumarin anticoagulants, resulting in a prolongation of prothrombin time. The effect of topical metronidazole on prothrombin time is not known.

Carcinogenesis, Mutagenesis, Impairment of Fertility:

Metronidazole has shown evidence of carcinogenic activity in a number of studies involving chronic, oral administration in mice and rats. Metronidazole has not been assessed for carcinogenic activity following topical administration. In several long term studies in mice, oral doses of approximately 200 mg/m^2/day (approximately 20 times the exposure of a patient that received the estimated maximum human topical daily dose (assuming 100% bioavailability and following normalization of the data on the basis of the body surface area)) or greater were associated with increase incidences of lung tumors in male mice and lymphomas in female mice. In several long-term studies in rats, oral administration of metronidazole resulted in increased incidences of mammary and hepatic tumors in female rats and testicular tumors and pituitary adenomas in male rats at dosages of approximately 1600 mg/m^2/day (approximately 170 times the exposure of a patient that received the estimated maximum human topical daily dose (assuming 100% bioavailability and following normalization of the data on the basis of the body surface area)) or greater. In another oral study, an increase of mammary tumors was observed in female rats that received approximately 160 mg/m^2/day (approximately 17 times the exposure of a patient that received the estimated maximum human topical daily dose (assuming 100% bioavailability and the following normalization of the data on the basis of the body surface area)).

Ultraviolet radiation-induced carcinogenesis was enhanced in albino mice by intraperitoneal injection of metronidazole at a dosage of 45 mg/m^2/day, 5 days per week for 10 weeks, as indicated by a decreased latency period to the development of skin neoplasms. It is unclear how this level of exposure compares to the clinical situation with respect to the concentration of the drug or metabolics in the skin. This study did not determine if metronidazole must be present during exposure to ultraviolet radiation in order to enhance tumor formation; metronidazole may promote tumor formation in cells that have previously been initiated by ultraviolet radiation.

Metronidazole exhibited mutagenic activity in several in vitro bacterial and mammalian assay systems. Intraperitoneal administration of metronidazole to mice resulted in a dosage-dependent increase in the incidence of chromosomal aberrations in peripheral lymphocytes was reported in patients with Crohn’s disease who were treated with metronidazole for 1 to 24 months at a dosage of 200 to 1200 mg/day. However, similar results were not observed in another study, in which humans were treated for 8 months.

In rats, oral metronidazole at a dosage of approximately 1800 mg/m^2/day (approximately 200 times the exposure of a patient that received the estimated maximum human topical daily dose (assuming 100% bioavailability and following normalization of the data on the basis of body surface area)) induced inhibition of spermatogenesis and severe testicular degeneration.

Pregnancy:

Teratogenic Effects: Pregnancy Category B: There are no adequate and well-controlled studies with the use of Metronidazole Topical Lotion in pregnant women. Metronidazole crosses the placental barrier and enters the fetal circulation rapidly. No fetotoxicity was observed after oral administration of metronidazole in rats or mice. However, because animal reproduction studies are not always predictive of human response and since oral metronidazole has been shown to be a carcinogen in some rodents, this drug should be used during pregnancy only if clearly needed.

Nursing Mothers:

After oral administration, metronidazole is secreted in breast milk in concentrations similar to those found in the plasma. Even though blood levels are significantly lower with topically applied metronidazole than those achieved after oral administration of metronidazole, a decision should be made whether to discontinue nursing or to discontinue the drug, taking into account the importance of the drug to the mother.

Pediatric Use:

Safety and effectiveness in pediatric patients have not been established.

ADVERSE REACTIONS

In a controlled clinical trial, safety data from 141 patients who used Metronidazole Topical Lotion (n=71), or the lotion vehicle (n=70), twice daily and experienced a local cutaneous adverse event which may or may not have been related to the treatments include: local allergic reaction, Metronidazole Topical Lotion 2 (3%), lotion vehicle 0; contact dermatitis, Metronidazole Topical Lotion 2 (3%), lotion vehicle 1 (1%); pruritus, Metronidazole Topical Lotion 1 (1%), lotion vehicle 0; skin discomfort (burning and stinging), Metronidazole Topical Lotion 1 (1%), lotion vehicle 2 (3%); erythema, Metronidazole Topical Lotion 4 (6%), lotion vehicle 0; dry skin, MetronidazoleTopical Lotion 0, lotion vehicle 1 (1%); and worsening of rosacea, Metronidazole Topical Lotion 1 (1%), lotion vehicle 7 (10%).

The following additional adverse experiences have been reported with the topical use of metronidazole: skin irritation, transient redness, metallic taste, tingling or numbness of extremities, and nausea.

DOSAGE AND ADMINISTRATION

Apply a thin layer to entire affected areas after washing. Use morning and evening or as directed by physician. Avoid application close to the eyes. Patients may use cosmetics after waiting for the MetronidazoleTopical Lotion to dry (not less than 5 minutes).

HOW SUPPLIED

Metronidazole Topical Lotion, 0.75% is supplied in the following size: 2 fl. oz. (59 mL) plastic bottle – NDC 68308-712-59

Storage:

Store at controlled room temperature 68° - 77°F (20° - 25°C). Protect from freezing.

Marketed By:
Mayne Pharma
Raleigh, NC 27609
1-844-825-8500
Product of Canada
P58196-0 Revised Sept 2024

PACKAGE LABEL

NDC 68308-712-59

Metronidazole Lotion
0.75%

Topical Lotion

Rx Only
2 FL OZ (59 mL)
maynepharma

STORE AT CONTROLLED ROOM TEMPERATURE 68° TO 77° (20°-25°C). PROTECT FROM FREEZING.
Distributed by:
Mayne Pharma
Raleigh, NC 27609
Product of Canada
P58197-0

FOR TOPICAL USE ONLY. NOT FOR OPHTHALMIC USE.

Usual Dosage: Apply a thin layer to entire affected areas after washing. Use morning and evening or as directed by physician. Avoid application close to the eyes.

Each gram contains:
Active: metronidazole, 0.75% w/w (7.5 mg).
Inactive: benzyl alcohol, carbomer 941, cyclomethicone, glycerin, glyceryl stearate, light mineral oil, PEG-100 stearate, polyethylene glycol 400, potassium sorbate, purified water, steareth-21, stearyl alcohol, and sodium hydroxide and/or lactic acid to adjust pH.
See lot number and expiration date on bottom of carton.